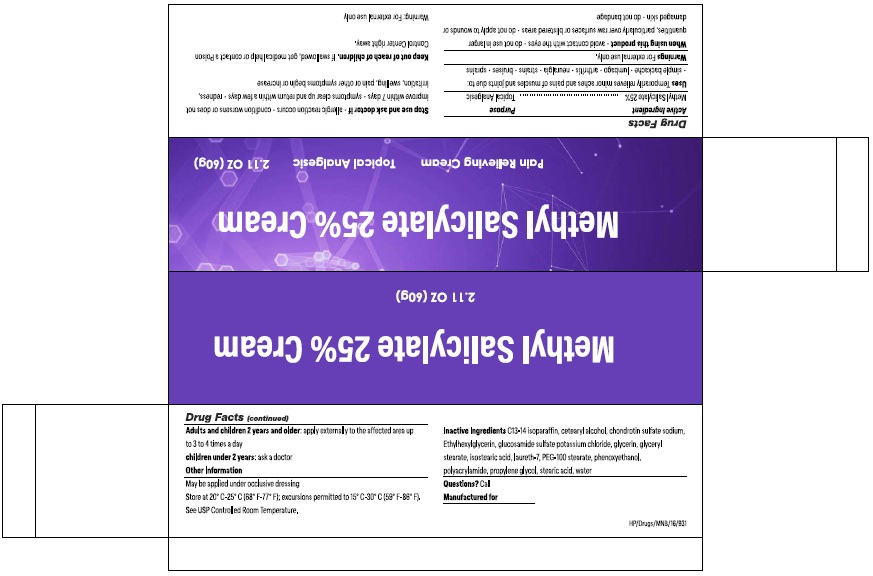 DRUG LABEL: Methyl Salicylate
NDC: 73492-273 | Form: CREAM
Manufacturer: ALAINA HEALTHCARE PRIVATE LIMITED
Category: otc | Type: HUMAN OTC DRUG LABEL
Date: 20251209

ACTIVE INGREDIENTS: METHYL SALICYLATE 25 g/60 g
INACTIVE INGREDIENTS: C13-14 ISOPARAFFIN; CETOSTEARYL ALCOHOL; CHONDROITIN SULFATE SODIUM, SHARK; ETHYLHEXYLGLYCERIN; GLUCOSAMINE SULFATE POTASSIUM CHLORIDE; GLYCERIN; GLYCERYL MONOSTEARATE; ISOSTEARIC ACID; LAURETH-7; PEG-100 MONOSTEARATE; PHENOXYETHANOL; POLYACRYLAMIDE (1500 MW); PROPYLENE GLYCOL; STEARIC ACID; WATER

Methyl Salicylate 25% Cream

Active Ingredient Purpose

Methyl Salicylate 25%........................................Topical Analgesic

Uses

Temporarily relieves minor aches and pains of muscles and joints due to:

- simple backache
- lumbago
- arthritis
- neuralgia
- strains
- bruises
- sprains

Warnings

For external use only.

When using this product

- avoid contact with the eyes
- do not use in larger quantities, particularly over raw surfaces or blistered areas
- do not apply to wounds or damaged skin
- do not bandage

Stop use and ask doctor if

- allergic reaction occurs
- condition worsens or does not improve within 7 days
- symptoms clear up and return within a few days
- redness, irritation, swelling, pain or other symptoms begin or increase

Keep out of reach of children.

If swallowed, get medical help or contact a Poison Control Center right away.

DOSAGE AND ADMINISTRATION

Adults and children 2 years and older:apply externally to the affected area up to 3 to 4 times a day
children under 2 years:ask a doctor

Other Information

May be applied under occlusive dressing

Store at 20° C-25° C (68° F-77° F); excursions permitted to 15° C-30° C (59° F-86° F). See USP Controlled Room Temperature.

Inactive Ingredients

C13-14 isoparaffin, cetearyl alcohol, chondrotin sulfate sodium, Ethylhexylglycerin, glucosamide sulfate potassium chloride, glycerin, glyceryl stearate, isostearic acid, laureth-7, PEG-100 stearate, phenoxyethanol, polyacrylamide, propylene glycol, stearic acid, water

Questions?Call

PRINCIPAL DISPLAY PANEL

Methyl Salicylate 25% Cream
Pain Relieving Cream
Topical Analgesic
2.11 oz (60g)